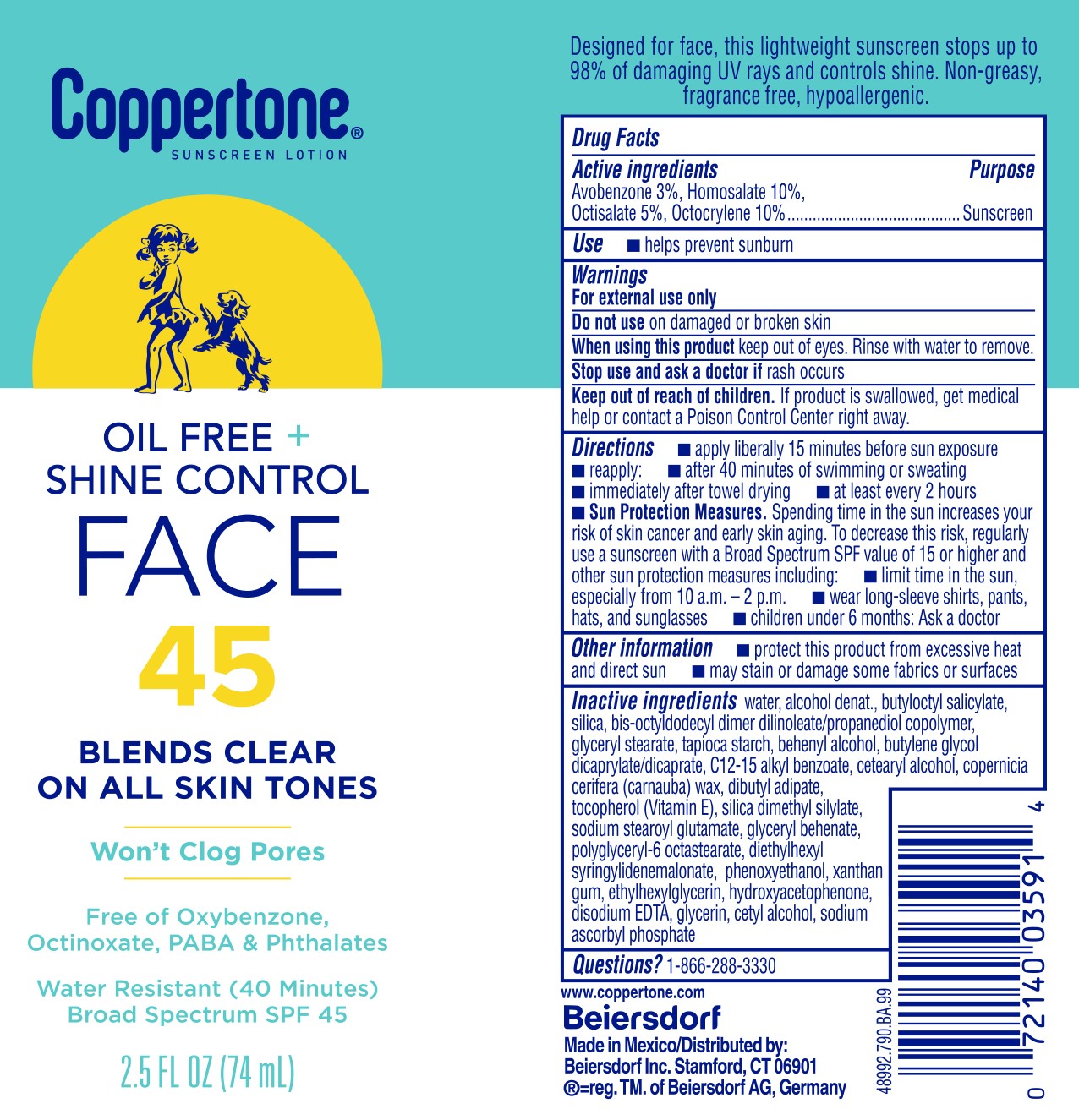 DRUG LABEL: Coppertone Oil Free and Shine Control Face Sunscreen SPF 45
NDC: 66800-8164 | Form: LOTION
Manufacturer: Beiersdorf Inc
Category: otc | Type: HUMAN OTC DRUG LABEL
Date: 20251217

ACTIVE INGREDIENTS: OCTISALATE 5 g/100 g; OCTOCRYLENE 10 g/100 g; AVOBENZONE 3 g/100 g; HOMOSALATE 10 g/100 g
INACTIVE INGREDIENTS: CARNAUBA WAX; DIBUTYL ADIPATE; SILICA DIMETHYL SILYLATE; GLYCERIN; WATER; CETOSTEARYL ALCOHOL; SODIUM STEAROYL GLUTAMATE; POLYGLYCERYL-6 ISOSTEARATE; BUTYLOCTYL SALICYLATE; DIETHYLHEXYL SYRINGYLIDENEMALONATE; ETHYLHEXYLGLYCERIN; PHENOXYETHANOL; XANTHAN GUM; DISODIUM EDTA-COPPER; CETYL ALCOHOL; SODIUM ASCORBYL PHOSPHATE; TITANIUM DIOXIDE; BUTYLENE GLYCOL DICAPRYLATE/DICAPRATE; ALCOHOL; ETHYLHEXYLGLYCERYL BEHENATE; HYDROXYACETOPHENONE; BIS-OCTYLDODECYL DIMER DILINOLEATE/PROPANEDIOL COPOLYMER; GLYCERYL STEARATE SE; STARCH, TAPIOCA; ALKYL (C12-15) BENZOATE; TOCOPHEROL; DOCOSANOL

Coppertone Oil Free + Shine Control Face Lotion SPF 45

Drug Facts

Purpose

Sunscreen

Active ingredients

Avobenzone 3%, Homosalate 10%, Octisalate 5%, Octocrylene 10%

Use

■ helps prevent sunburn

Warnings

For external use only

Do not useon damaged or broken skin

When using this productkeep out of eyes. Rinse with water to remove.

Stop use and ask a doctor ifrash occurs

Keep out of reach of children.If product is swallowed, get medical help or contact a Poison Control Center right away.

Directions

■ apply liberally 15 minutes before sun exposure

■ reapply:

■ after 40 minutes of swimming or sweating

■ immediately after towel drying

■ at least every 2 hours

■ Sun Protection Measures.Spending time in the sun increases your risk of skin cancer and early skin aging. To decrease this risk, regularly use a sunscreen with a Broad Spectrum SPF value of 15 or higher and other sun protection measures including:

■ limit time in the sun, especially from 10 a.m. – 2 p.m.

■ wear long-sleeve shirts, pants, hats, and sunglasses

■ children under 6 months: Ask a doctor

Other information

■ protect this product from excessive heat and direct sun

■ may stain or damage some fabrics or surfaces

Inactive ingredients

water, alcohol denat., butyloctyl salicylate, silica,bis-octyldodecyl dimer dilinoleate/propanediol copolymer, glyceryl stearate, tapioca starch, behenyl alcohol, butylene glycol dicaprylate/dicaprate, C12-15 alkyl benzoate, cetearyl alcohol, copernicia cerifera (carnauba) wax, dibutyl adipate, tocopherol (Vitamin E), silica dimethyl silylate, sodium stearoyl glutamate, glyceryl behenate, polyglyceryl-6 octastearate, diethylhexyl syringylidenemalonate, phenoxyethanol, xanthan gum, ethylhexylglycerin, hydroxyacetophenone, disodium EDTA, glycerin, cetyl alcohol, sodium ascorbyl phosphate

Questions?

1-866-288-3330

PACKAGE LABEL

Coppertone®Oil Free + Shine Control

Face

45

Blends Clear On All Skin Tones

Won't Clog Pores

Free of Oxybenzone, Octinoxate, PABA & Phthalates

Water Resistant (40 Minutes)

Broad Spectrum SPF 45